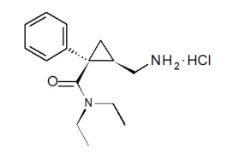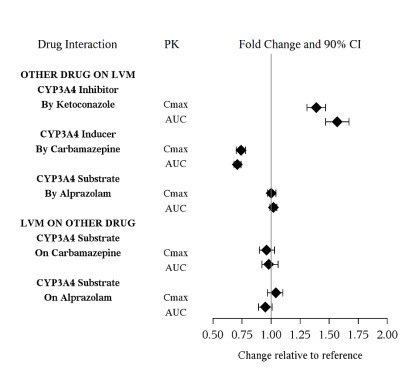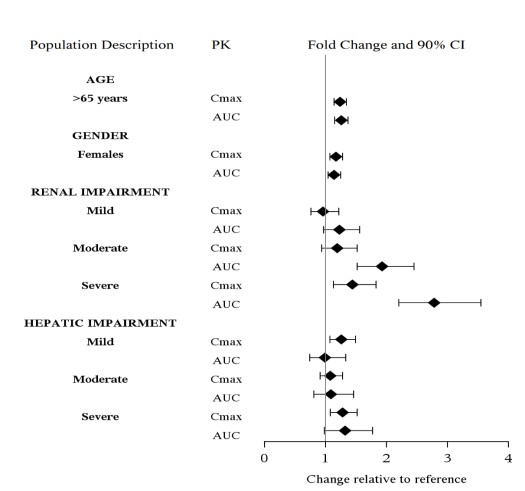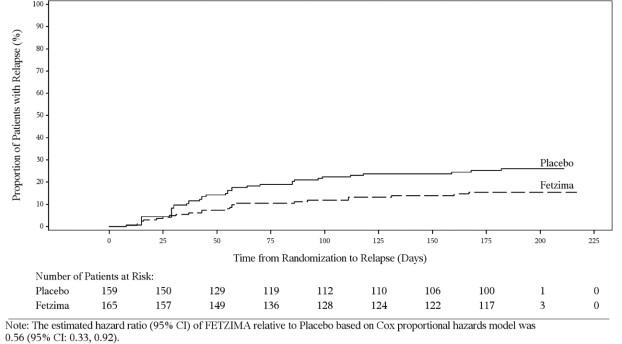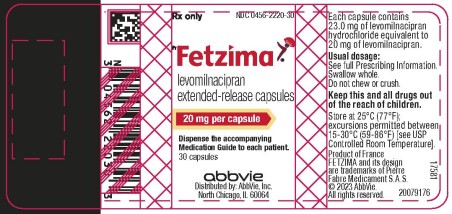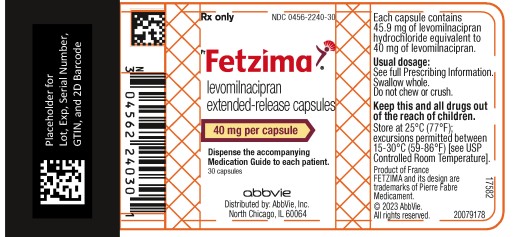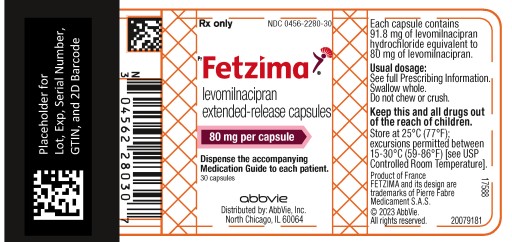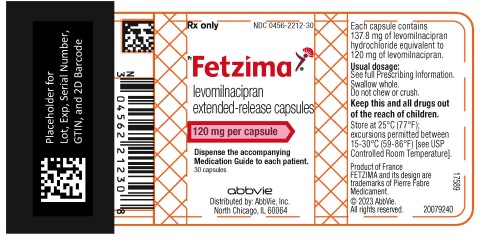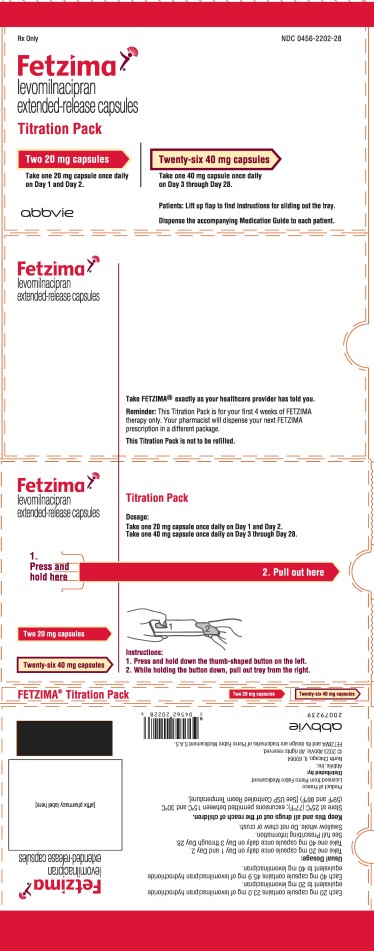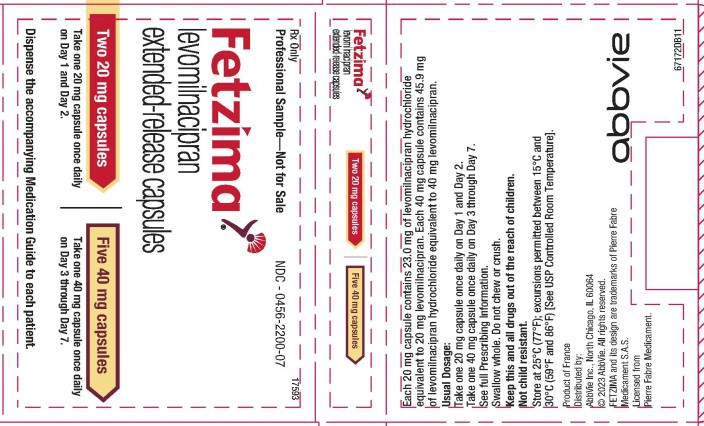 DRUG LABEL: Fetzima
NDC: 0456-2220 | Form: CAPSULE, EXTENDED RELEASE
Manufacturer: Allergan, Inc.
Category: prescription | Type: HUMAN PRESCRIPTION DRUG LABEL
Date: 20240430

ACTIVE INGREDIENTS: LEVOMILNACIPRAN HYDROCHLORIDE 20 mg/1 1
INACTIVE INGREDIENTS: SUCROSE; ETHYLCELLULOSE, UNSPECIFIED; TALC; POVIDONE, UNSPECIFIED; TRIETHYL CITRATE; HYPROMELLOSE, UNSPECIFIED; TITANIUM DIOXIDE; SHELLAC; FERROSOFERRIC OXIDE; FERRIC OXIDE YELLOW

HIGHLIGHTS OF PRESCRIBING INFORMATION

These highlights do not include all the information needed to use FETZIMA safely and effectively. See full prescribing information for FETZIMA.
FETZIMA® (levomilnacipran) extended-release capsules, for oral use
Initial U.S. Approval: 2009 (milnacipran)

RECENT MAJOR CHANGES

Warnings and Precautions (5.2, 5.5) | 8/2023

WARNING: SUICIDAL THOUGHTS AND BEHAVIORS

See full prescribing information for complete boxed warning.

Increased risk of suicidal thoughts and behavior in pediatric and young adult patients taking antidepressants. Closely monitor all antidepressant-treated patients for clinical worsening and emergence of suicidal thoughts and behaviors (5.1). FETZIMA is not approved for use in pediatric patients (8.4).

1 INDICATIONS AND USAGE

FETZIMA is a serotonin and norepinephrine reuptake inhibitor (SNRI) indicated for the treatment of Major Depressive Disorder (MDD) in adults (1).

Limitation of Use: FETZIMA is not approved for the management of fibromyalgia. The efficacy and safety of FETZIMA for the management of fibromyalgia have not been established (1).

2 DOSAGE AND ADMINISTRATION

- Recommended dosage: 40 mg to 120 mg once daily with or without food (2.1).
- Initial dosage is 20 mg once daily for 2 days and then increase to 40 mg once daily (2.1).
- Based on clinical response and tolerability, increase dose in increments of 40 mg at intervals of 2 or more days (2.1).
- The maximum recommended dosage is 120 mg once daily (2.1).
- Take capsules whole; do not open, chew or crush (2.1)
- Renal impairment (2.3):
  ○ Severe renal impairment: Maximum recommended dosage is 40 mg once daily.
  ○ Moderate renal impairment: Maximum recommended dosage is 80 mg once daily.
- Discontinuation: Reduce dose gradually whenever possible (2.4)

3 DOSAGE FORMS AND STRENGTHS

- Extended-release capsules: 20 mg, 40 mg, 80 mg, and 120 mg (3).

4 CONTRAINDICATIONS

- Hypersensitivity to levomilnacipran, milnacipran HCl, or any excipient in the FETZIMA formulation (4).
- Do not use MAOIs intended to treat psychiatric disorders with FETZIMA or within 7 days of stopping treatment with FETZIMA. Do not use FETZIMA within 14 days of stopping an MAOI intended to treat psychiatric disorders. In addition, do not start FETZIMA in a patient who is being treated with linezolid or intravenous methylene blue (4).

5 WARNINGS AND PRECAUTIONS

- Serotonin Syndrome: Increased risk when co-administered with other serotonergic agents, but also when taken alone. If it occurs, discontinue FETZIMA and serotonergic agents and initiate supportive treatment (5.2).
- Elevated Blood Pressure and Heart Rate: Control hypertension before initiating therapy with FETZIMA. Monitor blood pressure regularly during treatment (5.3, 5.4).
- Increased Risk of Bleeding: Concomitant use of NSAIDs, aspirin, other antiplatelet drugs, warfarin, and other anticoagulants may increase this risk (5.5).
- Angle Closure Glaucoma: Angle closure glaucoma has occurred in patients with untreated anatomically narrow angles treated with antidepressants (5.6).
- Urinary Hesitation or Retention: Can occur. If such symptoms occur, discontinue FETZIMA or consider other appropriate medical intervention (5.7).
- Activation of Mania/Hypomania: Screen patients for bipolar disorder. Caution patients about risk of activation of mania/hypomania (5.8).
- Seizures: Can occur. Use with caution in patients with a seizure disorder (5.9).
- Discontinuation Syndrome: Taper dose when possible and monitor for discontinuation symptoms (5.10).
- Hyponatremia: Can occur in association with SIADH (5.11).
- Sexual Dysfunction: FETZIMA may cause symptoms of sexual dysfunction (5.12).

6 ADVERSE REACTIONS

The most common adverse reactions (incidence ≥ 5% and at least twice the rate of placebo) are: nausea, constipation, hyperhidrosis, heart rate increase, erectile dysfunction, ejaculation disorder, tachycardia, vomiting, and palpitations (6.1).

To report SUSPECTED ADVERSE REACTIONS, contact AbbVie at 1-800-678-1605 or FDA at 1-800-FDA-1088 or www.fda.gov/medwatch.

7 DRUG INTERACTIONS

- Strong CYP3A4 inhibitors: Maximum recommended dosage is 80 mg once daily (7).

8 USE IN SPECIFIC POPULATIONS

- Pregnancy: Third trimester use may increase risk for symptoms of poor adaptation (respiratory distress, temperature instability, feeding difficulty, hypotonia, tremor, irritability) in the neonate. (8.1)

FULL PRESCRIBING INFORMATION

WARNING: SUICIDAL THOUGHTS AND BEHAVIORS

Antidepressants increased the risk of suicidal thoughts and behaviors in pediatric and young adult patients in short-term studies. Closely monitor all antidepressant-treated patients for clinical worsening, and for emergence of suicidal thoughts and behaviors [see Warnings and Precautions (5.1)].

FETZIMA is not approved for use in pediatric patients [see Use in Specific Populations (8.4)].

1 INDICATIONS AND USAGE

FETZIMA® is indicated for the treatment of major depressive disorder (MDD) in adults [see Clinical Studies (14)].

Limitation of Use: FETZIMA is not approved for the management of fibromyalgia. The efficacy and safety of FETZIMA for the management of fibromyalgia have not been established.

2 DOSAGE AND ADMINISTRATION

2.1 Recommended Dosage

The recommended dosage range for FETZIMA is 40 mg to 120 mg once daily, with or without food. FETZIMA should be initiated at 20 mg once daily for 2 days and then increased to 40 mg once daily. Based on clinical response and tolerability, FETZIMA may be increased in increments of 40 mg at intervals of 2 or more days. The maximum recommended dosage is 120 mg once daily.

Take FETZIMA at approximately the same time each day. Swallow FETZIMA whole; do not open, chew, or crush the capsule.

2.2 Screen for Bipolar Disorder Prior to Starting FETZIMA

Prior to initiating treatment with FETZIMA or another antidepressant, screen patients for a personal or family history of bipolar disorder, mania, or hypomania [see Warnings and Precautions (5.8)].

2.3 Dosage Recommendations for Patients with Renal Impairment

- End stage renal disease (ESRD): FETZIMA is not recommended;
- Severe renal impairment (creatinine clearance of 15 to 29 mL/min), the dosage should not exceed 40 mg once daily;
- Moderate renal impairment (creatinine clearance of 30 to 59 mL/min), the dosage should not exceed 80 mg once daily;
- Mild renal impairment (creatinine clearance of 60 to 89 mL/min): no dosage adjustment recommended [see Use in Specific Populations (8.7)].

2.4 Discontinuing Treatment with FETZIMA

Discontinuation symptoms have been reported with discontinuation of serotonergic drugs such as FETZIMA. Gradual dose reduction is recommended, instead of abrupt discontinuation, whenever possible. Monitor patients for these symptoms when discontinuing FETZIMA. If intolerable symptoms occur following a dose decrease or upon discontinuation of treatment, consider resuming the previously prescribed dose and decreasing the dose at a more gradual rate [see Warnings and Precautions (5.10)].

2.5 Switching a Patient To or From a Monoamine Oxidase Inhibitor (MAOI) Intended to Treat Psychiatric Disorders

At least 14 days must elapse between discontinuation of an MAOI intended to treat psychiatric disorders and initiation of therapy with FETZIMA. Conversely, at least 7 days should be allowed after stopping FETZIMA before starting an MAOI antidepressant [see Contraindications (4)].

2.6 Dosage Recommendations for Use with Strong CYP3A4 Inhibitors

The maximum recommended dosage of FETZIMA should not exceed 80 mg once daily when used with strong CYP3A4 inhibitors [see Drug Interactions (7.1)].

3 DOSAGE FORMS AND STRENGTHS

FETZIMA (levomilnacipran) is available as 20 mg, 40 mg, 80 mg, and 120 mg extended-release capsules.

Capsule Strength | Capsule Color/Shape | Capsule Markings
20 mg | yellow cap white body | black "FL" on cap black "20" on body
40 mg | yellow cap yellow body | black "FL" on cap black "40" on body
80 mg | pink cap white body | black "FL" on cap black "80" on body
120 mg | pink cap pink body | black "FL" on cap black "120" on body

4 CONTRAINDICATIONS

FETZIMA is contraindicated:

- in patients with hypersensitivity to levomilnacipran, milnacipran HCl, or to any excipient in the formulation.
- with the use of MAOIs intended to treat psychiatric disorders with FETZIMA or within 7 days of stopping treatment with FETZIMA is contraindicated because of an increased risk of serotonin syndrome. The use of FETZIMA within 14 days of stopping an MAOI intended to treat psychiatric disorders is also contraindicated [see Dosage and Administration (2.5) and Warnings and Precautions (5.2)].

Starting FETZIMA in a patient who is being treated with MAOIs such as linezolid or intravenous methylene blue is also contraindicated because of an increased risk of serotonin syndrome [see Dosage and Administration (2.6) and Warnings and Precautions (5.2)].

5 WARNINGS AND PRECAUTIONS

5.1 Suicidal Thoughts and Behaviors in Adolescents and Young Adults

In pooled analyses of placebo-controlled trials of antidepressant drugs (SSRIs and other antidepressant classes) that included approximately 77,000 adult patients and 4,500 pediatric patients, the incidence of suicidal thoughts and behaviors in antidepressant-treated patients aged 24 years and younger was greater than in placebo-treated patients. There was considerable variation in risk of suicidal thoughts and behaviors among drugs, but there was an increased risk identified in young patients for most drugs studied. There were differences in absolute risk of suicidal thoughts and behaviors across the different indications, with the highest incidence in patients with MDD. The drug-placebo differences in the number of cases of suicidal thoughts and behaviors per 1000 patients treated are provided in Table 1.

Table 1: Risk Differences of the Number of Patients of Suicidal Thoughts and Behavior in the Pooled Placebo-Controlled Trials of Antidepressants in Pediatric* and Adult Patients
Age Range | Drug-Placebo Difference in Number of Patients of Suicidal Thoughts or Behaviors per 1000 Patients Treated
 | Increases Compared to Placebo
<18 years old | 14 additional patients
18-24 years old | 5 additional patients
 | Decreases Compared to Placebo
25-64 years old | 1 fewer patient
≥65 years old | 6 fewer patients

*Fetzima is not approved for use in pediatric patients.

It is unknown whether the risk of suicidal thoughts and behaviors in children, adolescents, and young adults extends to longer-term use, i.e., beyond four months. However, there is substantial evidence from placebo-controlled maintenance trials in adults with MDD that antidepressants delay the recurrence of depression and that depression itself is a risk factor for suicidal thoughts and behaviors.

Monitor all antidepressant-treated patients for any indication for clinical worsening and emergence of suicidal thoughts and behaviors, especially during the initial few months of drug therapy, and at times of dosage changes. Counsel family members or caregivers of patients to monitor for changes in behavior and to alert the healthcare provider. Consider changing the therapeutic regimen, including possibly discontinuing FETZIMA, in patients whose depression is persistently worse, or who are experiencing emergent suicidal thoughts or behaviors.

5.2 Serotonin Syndrome

Serotonin-norepinephrine reuptake inhibitors (SNRIs), including FETZIMA, can precipitate serotonin syndrome, a potentially life-threatening condition. The risk is increased with concomitant use of other serotonergic drugs (including triptans, tricyclic antidepressants, fentanyl, lithium, tramadol, meperidine, methadone, tryptophan, buspirone, amphetamines, and St. John’s Wort) and with drugs that impair metabolism of serotonin, i.e., MAOIs [see Contraindications (4), Drug Interactions (7.1)]. Serotonin syndrome can also occur when these drugs are used alone.

Serotonin syndrome symptoms may include mental status changes (e.g., agitation, hallucinations, delirium, and coma), autonomic instability (e.g., tachycardia, labile blood pressure, dizziness, diaphoresis, flushing, hyperthermia), neuromuscular symptoms (e.g., tremor, rigidity, myoclonus, hyperreflexia, incoordination), seizures, and/or gastrointestinal symptoms (e.g., nausea, vomiting, diarrhea).

The concomitant use of FETZIMA with MAOIs is contraindicated. In addition, do not initiate FETZIMA in a patient who is being treated with MAOIs such as linezolid or intravenous methylene blue. No reports involved the administration of methylene blue by other routes (such as oral tablets or local tissue injection). If it is necessary to initiate treatment with a MAOI such as linezolid or intravenous methylene blue in a patient taking FETZIMA, discontinue FETZIMA before initiating treatment with the MAOI [see Dosage and Administration (2.5, 2.6) and Contraindications (4), Drug Interactions (7.1)].

Monitor all patients taking FETZIMA for the emergence of serotonin syndrome. Discontinue treatment with FETZIMA and any concomitant serotonergic agents immediately if the above events occur and initiate supportive symptomatic treatment. If concomitant use of FETZIMA with other serotonergic drugs is clinically warranted, inform patients of the increased risk for serotonin syndrome and monitor for symptoms.

5.3 Elevated Blood Pressure

SNRIs, including FETZIMA, have been associated with increases in blood pressure. Blood pressure should be measured prior to initiating treatment and periodically throughout FETZIMA treatment. Pre-existing hypertension should be controlled before initiating treatment with FETZIMA. Caution should be exercised in treating patients with pre-existing hypertension, cardiovascular, or cerebrovascular conditions that might be compromised by increases in blood pressure. For patients who experience a sustained increase in blood pressure while receiving FETZIMA, discontinuation or other appropriate medical intervention should be considered.

Table 2 shows the mean changes in blood pressure, sustained hypertension, and upward shifts in hypertensive status that were observed in FETZIMA-treated adult patients in the short-term placebo-controlled studies.

Table 2 Blood Pressure Mean Changes, Sustained Hypertension, and Upward Shifts in Hypertensive Status with FETZIMA (in Adults)
 |  | Placebo | FETZIMA 40 to 120 mg/day
Mean change from baseline to end of treatment, mm Hg
 | Systolic blood pressure (SBP) | -0.4 | 3.0
 | Diastolic blood pressure (DBP) | -0.0 | 3.2
Sustained Hypertension, % of patients
 | Broad Criteria: SBP ≥ 140 mm Hg and an increase ≥15 mm Hg OR DBP ≥ 90 mm Hg and an increase ≥ 10 mm Hg for at least 3 consecutive visits | 1.2 | 1.8
 | Strict Criteria: SBP ≥ 140 mm Hg and an increase ≥15 mm Hg AND DBP ≥ 90 mm Hg and an increase ≥ 10 mm Hg for at least 3 consecutive visits | 0.1 | 0.3
Upward Shifts in Hypertensive Statusa, % of patients
 | Normal/ Pre-hypertensive → Stage I/ Stage II | 7.1 | 10.4
a Normal Blood Pressure: SBP < 120 mm Hg and DBP < 80 mm Hg
Pre-hypertension: SBP ≥ 120 mm Hg and ≤ 139 mm Hg or DBP ≥ 80 mm Hg and ≤ 89 mm Hg
Stage I hypertension: SBP ≥ 140 mm Hg and ≤ 159 mm Hg or DBP ≥ 90 mm Hg and ≤ 99 mm Hg
Stage II hypertension: SBP ≥ 160 mm Hg or DBP ≥ 100 mm Hg

In the short-term, placebo-controlled MDD studies in adults, the mean increase from initiation of treatment in systolic BP was 3 mm Hg and diastolic BP was 3.2 mm Hg, as compared to no change in the placebo group. There were no dose-related changes in systolic and diastolic blood pressure observed.

In adult patients exposed to one-year, open-label treatment of FETZIMA (doses range from 40-120 mg once daily), the mean change from initiation of treatment in systolic BP was 3.9 mm Hg and diastolic BP was 3.1 mm Hg.

In short-term, placebo- and active-controlled MDD studies in pediatric patients 7 years to less than 18 years of age, treatment with FETZIMA was associated with the occurrence of new-onset hypertension (two systolic and/or diastolic BP measurements in the stage I hypertension range and/or one measurement in the stage II range) in 36.2% of treated patients compared with 20.7% of patients randomized to placebo. Elevations in either systolic or diastolic BP leading to measures at or above the stage II hypertension threshold occurred in 12.1% of pediatric patients treated with FETZIMA and 7.5% of patients randomized to placebo. Sustained hypertension (three or more consecutive systolic or diastolic BP measurements at or above the stage I hypertension threshold) occurred in 15% of pediatric patients treated with FETZIMA and 4% of patients randomized to placebo. The safety and effectiveness of FETZIMA have not been established in pediatric patients for the treatment of MDD.

In the short-term, placebo-controlled studies in adults, 11.6% of patients met orthostatic hypotension criteria (SBP or DBP) in the FETZIMA group compared to 9.7% in the placebo group. Orthostatic reductions of blood pressure ≥ 10 mm Hg in DBP occurred in 5.8%, 6.1%, and 9.8% of FETZIMA-treated patients with doses of 40, 80, and 120 mg/day respectively, compared to 6.2% of placebo-treated patients.

Concomitant use of FETZIMA with drugs that increase blood pressure and heart rate has not been evaluated and such combinations should be used with caution. Effects of FETZIMA on blood pressure in patients with significant hypertension or cardiac disease have not been systematically evaluated. FETZIMA should be used with caution in these patients.

5.4 Elevated Heart Rate

SNRIs, including FETZIMA, have been associated with increased heart rate. Heart rate should be measured prior to initiating treatment and periodically throughout FETZIMA treatment. Pre-existing tachyarrhythmias and other cardiac disease should be treated before starting therapy with FETZIMA. For patients who experience a sustained increase in heart rate while receiving FETZIMA, discontinuation or other appropriate medical intervention should be considered.

In short-term clinical studies, FETZIMA treatment was associated with a mean increase in heart rate of 7.4 beats per minute (bpm) compared to a mean decrease of 0.3 bpm in placebo-treated patients. Heart rate increase in FETZIMA-treated patients receiving doses of 40 mg, 80 mg, and 120 mg was 7.2, 7.2, and 9.1 bpm.

FETZIMA has not been systematically evaluated in patients with a cardiac rhythm disorder.

5.5 Increased Risk of Bleeding

Drugs that interfere with serotonin reuptake, including FETZIMA, may increase the risk of bleeding events. Concomitant use of aspirin, nonsteroidal anti-inflammatory drugs (NSAIDs), warfarin, and other anticoagulants may add to this risk. Case reports and epidemiological studies (case-control and cohort design) have demonstrated an association between use of drugs that interfere with serotonin reuptake and the occurrence of gastrointestinal bleeding. Based on data from the published observational studies, exposure to SNRIs, particularly in the month before delivery, has been associated with a less than 2-fold increase in the risk of postpartum hemorrhage [see Use in Specific Populations (8.1)]. Bleeding events related to SSRIs and SNRIs have ranged from ecchymosis, hematoma, epistaxis, and petechiae to life-threatening hemorrhages.

Inform patients about the increased risk of bleeding associated with the concomitant use of FETZIMA and NSAIDs, aspirin, or other drugs that affect coagulation [see Drug Interactions (7.1)].

5.6 Angle Closure Glaucoma

The pupillary dilation that occurs following use of many antidepressant drugs including FETZIMA may trigger an angle closure attack in a patient with anatomically narrow angles who does not have a patent iridectomy. Avoid use of antidepressants, including FETZIMA, in patients with anatomically narrow angles.

5.7 Urinary Hesitation or Retention

The noradrenergic effect of SNRIs including FETZIMA, can affect urethral resistance. In the controlled short-term studies, urinary hesitation occurred in 4%, 5%, and 6% of FETZIMA-treated patients receiving doses of 40, 80, and 120 mg, respectively, compared to no patients in the placebo group. Caution is advised in the use of FETZIMA in patients prone to obstructive urinary disorders. If symptoms of urinary hesitation, urinary retention, or dysuria develop during treatment with FETZIMA, consideration should be given to the possibility that they might be drug-related, and discontinuation or other appropriate medical intervention should be considered.

5.8 Activation of Mania/Hypomania

Symptoms of mania/hypomania were reported in 0.2% of FETZIMA-treated patients and 0.2% of placebo-treated patients in clinical studies. Activation of mania/hypomania has also been reported in a small proportion of patients with mood disorders who were treated with other antidepressants. Prior to initiating treatment with FETZIMA, screen patients for any personal or family history of bipolar disorder, mania, or hypomania.

5.9 Seizures

One case of seizure has been reported in pre-marketing clinical studies with FETZIMA. FETZIMA has not been systematically evaluated in patients with a seizure disorder. Patients with a history of seizures were excluded from clinical studies. FETZIMA should be prescribed with caution in patients with a seizure disorder.

5.10 Discontinuation Syndrome

There have been reports of adverse events occurring upon discontinuation of serotonergic antidepressants, particularly when discontinuation is abrupt, including the following: dysphoric mood, irritability, agitation, dizziness, sensory disturbances (e.g., paresthesia, such as electric shock sensations), anxiety, confusion, headache, lethargy, emotional lability, insomnia, hypomania, tinnitus, and seizures. While these events are generally self-limiting, there have been reports of serious discontinuation symptoms.

Monitor patients for these symptoms when discontinuing FETZIMA. Reduce the dose gradually whenever possible. If intolerable symptoms occur following a decrease in the dose or upon discontinuation of treatment, consider resuming the previously prescribed dose. Subsequently, the dose may be decreased, but at a more gradual rate [see Dosage and Administration (2.4)].

5.11 Hyponatremia

Hyponatremia may occur as a result of treatment with SSRIs and SNRIs, including FETZIMA. In many cases, hyponatremia appears to be the result of the syndrome of inappropriate antidiuretic hormone secretion (SIADH). Cases with serum sodium lower than 110 mmol/L have been reported. Elderly patients may be at greater risk of developing hyponatremia with SSRIs and SNRIs. Also, patients taking diuretics or who are otherwise volume depleted can be at greater risk. FETZIMA should be discontinued in patients with symptomatic hyponatremia and appropriate medical intervention should be instituted. Signs and symptoms of hyponatremia include headache, difficulty concentrating, memory impairment, confusion, weakness, and unsteadiness, which can lead to falls. Signs and symptoms associated with more severe and/or acute cases have included hallucination, syncope, seizure, coma, respiratory arrest, and death.

5.12 Sexual Dysfunction

Use of SNRIs, including FETZIMA, may cause symptoms of sexual dysfunction [see Adverse Reactions (6.1)]. In male patients, SNRI use may result in ejaculatory delay or failure, decreased libido, and erectile dysfunction. In female patients, SNRI use may result in decreased libido and delayed or absent orgasm.

It is important for prescribers to inquire about sexual function prior to initiation of FETZIMA and to inquire specifically about changes in sexual function during treatment, because sexual function may not be spontaneously reported. When evaluating changes in sexual function, obtaining a detailed history (including timing of symptom onset) is important because sexual symptoms may have other causes, including the underlying psychiatric disorder. Discuss potential management strategies to support patients in making informed decisions about treatment.

6 ADVERSE REACTIONS

The following adverse reactions are discussed in greater detail in other sections of the label.

- Hypersensitivity [see Contraindications (4)]
- Suicidal Thoughts and Behaviors in Adolescents and Young Adults [see Warnings and Precautions (5.1)]
- Serotonin Syndrome [see Warnings and Precautions (5.2)]
- Elevated Blood Pressure [see Warnings and Precautions (5.3)]
- Elevated Heart Rate [see Warnings and Precautions (5.4)]
- Increased Risk of Bleeding [see Warnings and Precautions (5.5)]
- Angle Closure Glaucoma [see Warnings and Precautions (5.6)]
- Urinary Hesitation or Retention [see Warnings and Precautions (5.7)]
- Activation of Mania/Hypomania [see Warnings and Precautions (5.8)]
- Seizure [see Warnings and Precautions (5.9)]
- Discontinuation Syndrome [see Warnings and Precautions (5.10)]
- Hyponatremia [see Warnings and Precautions (5.11)]
- Sexual Dysfunction [see Warnings and Precautions (5.12)]

6.1 Clinical Studies Experience

Because clinical trials are conducted under widely varying conditions, adverse reaction rates observed in the clinical trials of a drug cannot be directly compared to rates in the clinical studies of another drug and may not reflect the rates observed in clinical practice.

Patient exposure

The safety of FETZIMA was evaluated in 3,317 patients (18 to 78 years of age) diagnosed with MDD who participated in clinical studies, representing 1,186 patient-years of exposure. Among the 3,317 FETZIMA-treated patients, 1,583 were exposed to FETZIMA in short-term, placebo-controlled studies. There were 825 patients who continued from short-term studies into a one-year, open-label extension study.

Of the 3,317 patients exposed to at least one dose of FETZIMA, 895 patients were exposed to FETZIMA for at least 6 months and 367 were exposed for one year. In these studies, FETZIMA was given at doses ranging from 40 mg to 120 mg once daily and was given without regard to food.

Adverse reactions reported as reasons for discontinuation of treatment

In the short-term placebo-controlled pre-marketing studies for MDD, 9% of the 1,583 patients who received FETZIMA (40 mg to 120 mg) discontinued treatment due to an adverse reaction, compared with 3% of the 1,040 placebo-treated patients in those studies. The most common adverse reaction leading to discontinuation in at least 1% of the FETZIMA-treated patients in the short-term placebo-controlled studies was nausea (1.5%).

Common adverse reactions in placebo-controlled MDD studies

The most commonly observed adverse reactions in FETZIMA-treated MDD patients in placebo-controlled studies (incidence ≥ 5% and at least twice the rate of placebo) were: nausea, constipation, hyperhidrosis, heart rate increased, erectile dysfunction, ejaculation disorder, tachycardia, vomiting, and palpitations.

Table 3 shows the incidence of adverse reactions that occurred in ≥ 2% of FETZIMA-treated MDD patients and at least twice the rate of placebo in the placebo-controlled studies.

Table 3 Adverse Reactions Occurring in ≥ 2% of FETZIMA-treated Patients and at Least Twice the rate of Placebo-treated Patients in Pooled MDD Studies
System Organ Class Preferred Term | Placebo (N =1040) % | FETZIMA 40 mg to 120 mg per day (N = 1583) %
Gastrointestinal disorders
Nausea | 6 | 17
Constipation | 3 | 9
Vomiting | 1 | 5
Cardiac disorders
Tachycardiaa | 2 | 6
Palpitations | 1 | 5
Reproductive system and breast disordersb
Erectile dysfunctionc | 1 | 6
Testicular paind | <1 | 4
Ejaculation disordere | <1 | 5
Investigations
Heart rate increasedf | 1 | 6
Blood pressure increasedg | 1 | 3
Renal and urinary disorders
Urinary hesitation | 0 | 4
Skin and subcutaneous tissue disorders
Hyperhidrosis | 2 | 9
Rashh | 0 | 2
Vascular disorders
Hot flush | 1 | 3
Hypotensioni | 1 | 3
Hypertensionj | 1 | 3
Metabolism and nutrition disorders
Decreased appetite | 1 | 3
a Tachycardia also includes: sinus tachycardia and postural orthostatic tachycardia syndrome
b Percentage is relative to the number of patients in the associated demographic sex category. Fewer than 2% of FETZIMA-treated MDD female patients in placebo-controlled clinical studies reported adverse events related to sexual function.
c Erectile dysfunction includes: erectile dysfunction, organic erectile dysfunction, and psychogenic erectile dysfunction
d Testicular pain includes: testicular pain, epididymitis, and seminal vesiculitis
e Ejaculation disorder includes: ejaculation disorder, ejaculation delayed, ejaculation failure, and premature ejaculation
f Heart rate increased also includes: orthostatic heart rate response increased
g Blood pressure increased also includes: blood pressure systolic increased, blood pressure diastolic increased, and blood pressure orthostatic increased
h Rash also includes: rash generalized, rash maculo-papular, rash erythematous, and rash macular
i Hypotension also includes: orthostatic hypotension and dizziness postural
j Hypertension also includes: labile hypertension
N = number of patients in the Safety Population

Dose-related adverse reactions

In pooled data from the short-term placebo-controlled fixed-dose studies, there were no dose-related adverse reactions (greater than 2% overall incidence) in patients treated with FETZIMA across the dose range 40 mg to 120 mg once daily, with the exception of erectile dysfunction and urinary hesitation (see Table 4).

Table 4 Dose-Related Adverse Reactions
System Organ Class Preferred Term | Placebo (N = 362) % | FETZIMA
 |  | 40 mg per day (N = 366) % | 80 mg per day (N = 367) % | 120 mg per day (N = 180) %
Urinary hesitation | 0 | 4 | 5 | 6
Erectile dysfunctiona | 2 | 6 | 8 | 10
a Percentage is relative to the number of male patients.
N = number of patients in the Safety Population

Other adverse reactions observed in clinical studies

Other infrequent adverse reactions, not described elsewhere in the label, occurring at an incidence of < 2% in MDD patients treated with FETZIMA were:

Cardiac disorders: Angina pectoris; Supraventricular and Ventricular extrasystoles

Eye disorders: Dry eye; Vision blurred; Conjunctival hemorrhage

General disorders: Chest pain; Thirst

Gastrointestinal disorders: Abdominal pain; Flatulence

Investigations disorders: Blood cholesterol increased; Liver function test abnormal

Nervous System disorders: Migraine; Paraesthesia; Syncope; Extrapyramidal disorder

Psychiatric disorders: Agitation; Anger; Bruxism; Panic attack; Tension; Aggression

Renal and Urinary disorder: Pollakiuria; Hematuria; Proteinuria

Respiratory, thoracic and mediastinal disorders: Yawning

Skin and subcutaneous tissue disorders: Dry skin; Pruritus; Urticaria

6.2 Postmarketing Experience

The following adverse reaction has been identified during post-approval use of FETZIMA or other selective serotonin and norepinephrine reuptake inhibitors. Because these reactions are reported voluntarily from a population of uncertain size, it is not always possible to reliably estimate their frequency or establish a causal relationship to drug exposure.

Cardiac disorders: Takotsubo cardiomyopathy

Respiratory, thoracic and mediastinal disorders: Anosmia, Hyposmia

7 DRUG INTERACTIONS

7.1 Drugs Having Clinically Important Interactions with FETZIMA

Table 5 includes clinically important drug interactions with FETZIMA.

Table 5: Clinically Important Drug Interactions with FETZIMA
Monoamine Oxidase Inhibitors (MAOIs)
Clinical Impact: | Concomitant use of SSRIs and SNRIs including FETZIMA with MAOIs increases the risk of serotonin syndrome.
Intervention: | Concomitant use of FETZIMA is contraindicated:; - With an MAOI intended to treat psychiatric disorders or within 7 days of stopping treatment with FETZIMA. - Within 14 days of stopping an MAOI intended to treat psychiatric disorders - In a patient who is being treated with linezolid or intravenous methylene blue; [see Dosage and Administration (2.5, 2.6), Contraindications (4), and Warnings and Precautions (5.2)].
Examples: | selegiline, tranylcypromine, isocarboxazid, phenelzine, linezolid, methylene blue
Other Serotonergic Drugs
Clinical Impact: | Concomitant use of FETZIMA with other serotonergic drugs increases the risk of serotonin syndrome.
Intervention: | Monitor for symptoms of serotonin syndrome when FETZIMA is used concomitantly with other drugs that may affect the serotonergic neurotransmitter systems. If serotonin syndrome occurs, immediately discontinue FETZIMA and/or concomitant serotonergic drugs [see Dosage and Administration (2.5, 2.6), Contraindications (4), and Warnings and Precautions (5.2)].
Examples: | other SNRIs, SSRIs, triptans, tricyclic antidepressants, opioids, lithium, buspirone, amphetamines, tryptophan, and St. John's Wort
Drugs that Interfere with Hemostasis
Clinical Impact: | Concomitant use of FETZIMA with an antiplatelet or anticoagulant drug may potentiate the risk of bleeding. This may be due to the effect of FETZIMA on the release of serotonin by platelets.
Intervention: | Closely monitor for bleeding for patients receiving an antiplatelet or anticoagulant drug when FETZIMA is initiated or discontinued [see Warnings and Precautions (5.5)].
Examples: | NSAIDs, aspirin, and warfarin
Strong CYP3A4 Inhibitors
Clinical Impact: | Concomitant use of FETZIMA with strong CYP3A4 inhibitors increases levomilnacipran exposure [see Pharmacokinetics (12.3)].
Intervention: | The dose of FETZIMA should not exceed 80 mg once daily when used with strong CYP3A4 inhibitors [see Dosage and Administration (2.6).
Examples: | Ketoconazole, itraconazole, clarithromycin
Alcohol
Clinical Impact: | Concomitant use of FETZIMA and alcohol may result in accelerated release of levomilnacipran.
Intervention: | Avoid concomitant use of FETZIMA and alcohol [see Clinical Pharmacology (12.3)].

8 USE IN SPECIFIC POPULATIONS

8.1 Pregnancy

Pregnancy Exposure Registry

There is a pregnancy exposure registry that monitors pregnancy outcomes in women exposed to antidepressants during pregnancy. Healthcare providers are encouraged to advise patients to register by calling the National Pregnancy Registry for Antidepressants at 1-844-405-6185 or visiting online at https://womensmentalhealth.org/research/pregnancyregistry/antidepressants.

Risk Summary

Based on data from published observational studies, exposure to SNRIs, particularly in the month before delivery, has been associated with a less than 2-fold increase in the risk of postpartum hemorrhage [see Warnings and Precautions (5.5) and Clinical Considerations].

The available data on FETZIMA use in pregnant women are insufficient to evaluate for a drug-associated risk of major birth defects, miscarriage, or adverse maternal or fetal outcomes. There are risks associated with untreated depression in pregnancy and with exposure to SNRIs and SSRIs, including FETZIMA, during pregnancy (see Clinical Considerations).

In animal reproduction studies, levomilnacipran was not associated with malformations in rats or rabbits when given during the period of organogenesis at doses up to 8 or 16 times the maximum recommended human dose (MRHD) of 120 mg on a mg/m^2 basis, respectively. However, an increase in early post-natal rat pup mortality was seen at a dose equivalent to 5 times the MRHD given during pregnancy and lactation (see Data).

The estimated background risk of major birth defects and miscarriage for the indicated population is unknown. All pregnancies have a background risk of birth defect, loss, or other adverse outcomes. In the U.S. general population, the estimated background risk of major birth defects and miscarriage in clinically recognized pregnancies is 2 to 4% and 15 to 20%, respectively.

Clinical Considerations

Disease-associated maternal and/or embryo/fetal risk

Women who discontinued antidepressants during pregnancy were more likely to experience a relapse of major depression than women who continued antidepressants. This finding is from a prospective, longitudinal study that followed 201 pregnant women with a history of major depressive disorder who were euthymic and taking antidepressants at the beginning of pregnancy. Consider the risk of untreated depression when discontinuing or changing treatment with antidepressant medication during pregnancy and postpartum.

Maternal Adverse Reactions

Use of FETZIMA in the month before delivery may be associated with an increased risk of postpartum hemorrhage [see Warnings and Precautions (5.5)].

Fetal/Neonatal adverse reactions

Neonates exposed to SNRIs or SSRIs, including FETZIMA, late in the third trimester have developed complications requiring prolonged hospitalization, respiratory support, and tube feeding. Such complications can arise immediately upon delivery. Reported clinical findings have included respiratory distress, cyanosis, apnea, seizures, temperature instability, feeding difficulty, vomiting, hypoglycemia, hypotonia, hypertonia, hyperreflexia, tremor, jitteriness, irritability, and constant crying. These findings are consistent with either direct toxic effect of SSRIs and SNRIs or possibly, a drug discontinuation syndrome. It should be noted that, in some cases, the clinical picture is consistent with serotonin syndrome [see Warnings and Precautions (5.2 and 5.10)].

Data

Animal Data

No malformations were observed when levomilnacipran was administered to pregnant rats or rabbits during the period of organogenesis at oral doses up to 100 mg/kg/day. This dose is 8 and 16 times (in rats and rabbits, respectively) the maximum recommended human dose (MRHD) of 120 mg on a mg/m^2 basis. Fetal body weights were reduced in rats, and skeletal ossification was delayed in both rats and rabbits at this dose; these effects were not observed in either species at doses up to 30 mg/kg/day, 2.4 times the MRHD in rats or 5 times the MRHD in rabbits on a mg/m^2 basis.

When levomilnacipran was administered to pregnant rats at an oral dose of 60 mg/kg/day, 5 times the MRHD, during organogenesis and throughout pregnancy and lactation, there was an increase in early postnatal pup mortality; no pup mortality was seen at 20 mg/kg/day, 1.6 times the MRHD on a mg/m^2 basis. Among the surviving pups, pre- and post-weaning pup weight gain was reduced up to at least 8 weeks of age; however, physical and functional development, including reproductive performance of the progeny, was not affected. The effects on body weight gain were not seen at 7 mg/kg/day, 0.6 times the MRHD on a mg/m^2 basis.

8.2 Lactation

Risk Summary

There are no available data on the presence of levomilnacipran in human milk; however, racemic milnacipran is present in human milk (see Data). There are no reports on the effects of levomilnacipran or milnacipran on the breastfed infant or the effects on milk production. However, there are reports of agitation, irritability, poor feeding and poor weight gain in infants exposed to SSRIs or SNRIs through breast milk (see Clinical Considerations). The developmental and health benefits of breastfeeding should be considered along with the mother’s clinical need for FETZIMA and any potential adverse effects on the breastfed child from FETZIMA or from the underlying maternal conditions.

Clinical Considerations

Infants exposed to FETZIMA should be monitored for agitation, irritability, poor feeding and poor weight gain.

Data

Milnacipran, a racemic mixture that contains levomilnacipran (the 1S,2R-enantiomer of milnacipran), is present in the milk of lactating women treated with milnacipran. In a lactation pharmacokinetic study with milnacipran, a single, oral dose of 50 mg milnacipran HCl tablet was administered to 8 lactating women who were at least 12 weeks postpartum and weaning their infants. The milk/plasma AUC ratio of milnacipran was 1.85 ± 0.38. The maximum estimated weight-adjusted daily infant dose for milnacipran from breast milk (assuming mean milk consumption of 150 mL/kg/day) was 5% of the maternal weight-adjusted dose based on peak plasma concentrations.

8.4 Pediatric Use

The safety and effectiveness of FETZIMA have not been established in pediatric patients for the treatment of major depressive disorder (MDD).

The safety and efficacy of FETZIMA were evaluated in two randomized, double-blind, placebo- and active-controlled 8-week trials in pediatric patients with MDD, one in patients 7 to 17 years of age (flexible-dose study) and the other in patients 12 to 17 years of age (fixed-dose study). The primary efficacy endpoint for both studies was the change from baseline to week 8 in the Children’s Depression Rating Scale-Revised (CDRS-R) total score. The CDRS-R assesses the severity of depression and change in depressive symptoms in children and adolescents with depression. FETZIMA was not superior to placebo in either study. The most commonly observed adverse reactions in pediatric patients 7 to 17 years of age randomized to FETZIMA were similar to those observed in adults [see Adverse Reactions (6.1)].

FETZIMA was associated with an increase in blood pressure in placebo- and active-controlled trials in pediatric patients with MDD. Increases in blood pressure in pediatric patients treated with FETZIMA led to a higher proportion of pediatric patients developing new-onset and sustained hypertension when compared to adults [see Warnings and Precautions (5.3)].

Antidepressants increase the risk of suicidal thoughts and behaviors in pediatric patients [see Boxed Warning, Warnings and Precautions (5.1), and Adverse Reactions (6.1)].

Juvenile Animal Toxicity Data

In a juvenile animal study, male and female rats were treated with 10, 35, or 120 mg/kg/day of levomilnacipran by oral gavage from post-natal day 21 to 90. At 120 mg/kg/day, there was a decrease in bone mineral density in both males and females and a decrease in mean tibia length in females. These effects were not completely resolved at the end of the recovery period. There was a delay in sexual maturation in females treated with 120 mg/kg/day; however, there was no effect on fertility. The no observed adverse effect level (NOAEL) for all these findings was 35 mg/kg/day.

8.5 Geriatric Use

No dose adjustment is recommended on the basis of age [see Clinical Pharmacology (12.3)].

Of the total number of patients in the 8-week clinical studies of FETZIMA, 2.8% of patients were age 65 or older.

Because levomilnacipran is predominantly excreted by the kidney, renal clearance of levomilnacipran should be considered when determining the dose [see Dosage and Administration (2.3)].

SNRIs, including FETZIMA, have been associated with cases of clinically significant hyponatremia in elderly patients, who may be at greater risk for this adverse reaction [see Warnings and Precautions (5.11)].

8.6 Hepatic Impairment

Dose adjustment is not recommended in patients with mild (Child-Pugh score of 1-6), moderate (Child-Pugh score of 7-9), or severe (Child-Pugh score of 10-13) hepatic impairment [see Clinical Pharmacology (12.3)].

8.7 Renal Impairment

Renal excretion plays a predominant role in the elimination of levomilnacipran.

FETZIMA is not recommended for use in patients with end stage renal disease.

Dosing adjustment is recommended for patients with moderate (creatinine clearance of 30 to 59 mL/min) or severe (creatinine clearance of 15 to 29 mL/min) renal impairment [see Dosage and Administration (2.3) and Clinical Pharmacology (12.3)].

Dose adjustment is not recommended for patients with mild (creatinine clearance of 60 to 89 mL/min) renal impairment [see Clinical Pharmacology (12.3)].

9 DRUG ABUSE AND DEPENDENCE

9.1 Controlled Substance

FETZIMA is not a controlled substance.

9.2 Abuse

FETZIMA has not been systematically studied in animals or humans for its potential for abuse. There was no evidence suggestive of drug-seeking behavior in the clinical studies. It is not possible to predict on the basis of clinical experience the extent to which a CNS active drug will be misused, diverted, and/or abused once marketed. Consequently, physicians should carefully evaluate patients for a history of drug abuse and follow such patients closely, observing them for signs of misuse or abuse of FETZIMA (e.g., development of tolerance or drug-seeking behavior).

9.3 Dependence

FETZIMA has not been systematically studied in animals or humans for its potential for dependence.

10 OVERDOSAGE

10.1 Human Experience

There is limited clinical experience with FETZIMA overdose in humans. In clinical studies, cases of ingestions up to 360 mg daily were reported with none being fatal.

10.2 Management of Overdose

No specific antidotes for FETZIMA are known. In managing overdose, provide supportive care, including close medical supervision and monitoring, and consider the possibility of multiple drug involvement. In case of an overdose, consult a Certified Poison Control Center (1-800-222-1222) for up-to-date guidance and advice. The high volume of distribution of levomilnacipran suggests that dialysis will not be effective in reducing levomilnacipran plasma concentrations.

11 DESCRIPTION

FETZIMA contains levomilnacipran, a selective serotonin and norepinephrine reuptake inhibitor (SNRI), in the form of hydrochloride salt with the chemical name of levomilnacipran hydrochloride is (1S,2R)-2-(aminomethyl)-N,N-diethyl-1-phenylcyclopropanecarboxamide hydrochloride. Its empirical formula is C15H22N2O∙HCl and its molecular weight is 282.8 g/mol. Levomilnacipran (Initial US approval: 2013) is the 1S,2R-enantiomer of milnacipran. The chemical structure of levomilnacipran hydrochloride is:

FETZIMA extended-release capsules are intended for oral administration. Each FETZIMA capsule contains 23.0, 45.9, 91.8, or 137.8 mg of levomilnacipran hydrochloride equivalent to 20, 40, 80, or 120 mg of levomilnacipran, respectively.

Inactive ingredients include ethylcellulose, hypromellose, povidone, sugar spheres, talc, titanium dioxide, and triethyl citrate. Inactive ingredients also include black iron oxide, red iron oxide (80 mg and 120 mg capsules only), shellac glaze, and yellow iron oxide (20 mg and 40 mg capsules only).

12 CLINICAL PHARMACOLOGY

12.1 Mechanism of Action

The exact mechanism of the antidepressant action of levomilnacipran is unknown, but is thought to be related to the potentiation of serotonin and norepinephrine in the central nervous system, through inhibition of reuptake at serotonin and norepinephrine transporters. Non-clinical studies have shown that levomilnacipran is a potent and selective serotonin and norepinephrine reuptake inhibitor (SNRI).

12.2 Pharmacodynamics

Levomilnacipran binds with high affinity to the human serotonin (5-HT) and norepinephrine (NE) transporters (Ki = 11 and 91 nM, respectively) and potently inhibits 5-HT and NE reuptake (IC50 = 16-19 and 11 nM, respectively). Levomilnacipran lacks significant affinity for any other receptors, ion channels or transporters tested in vitro, including serotonergic (5HT1-7), α- and β- adrenergic, muscarinic, or histaminergic receptors and Ca^2+, Na+, K+ or Cl- channels. Levomilnacipran did not inhibit monoamine oxidase (MAO).

Cardiovascular Electrophysiology

At a dose 2.5 times the maximum recommended dose, levomilnacipran does not prolong QTc to any clinically relevant extent.

12.3 Pharmacokinetics

The concentration of levomilnacipran at steady state is proportional to dose when administered from 25 mg to 300 mg (2.5 times the maximum recommended dosage of FETZIMA) once daily. Steady-state concentrations of levomilnacipran are predictable from single-dose data. After daily dosing of FETZIMA 120 mg, the mean Cmax value is 341 ng/mL, and the mean steady-state AUC value is 5196 ng·h/mL. Interconversion between levomilnacipran and its stereoisomer does not occur in humans.

Absorption

The relative bioavailability of levomilnacipran after administration of FETZIMA was 92% when compared to oral solution. The median time to peak concentration (Tmax) of levomilnacipran is 6-8 hours after oral administration.

Effect of Food

Levomilnacipran concentration was not significantly affected when FETZIMA was administered with food.

Distribution

Levomilnacipran is widely distributed with an apparent volume of distribution of 387-473 L; plasma protein binding is 22% over concentration range of 10 to 1000 ng/mL.

Elimination

Following an oral administration, the mean apparent total clearance of levomilnacipran is 21-29 L/h. The apparent terminal elimination half-life of levomilnacipran is approximately 12 hours.

Metabolism

Levomilnacipran undergoes desethylation to form desethyl levomilnacipran and hydroxylation to form p-hydroxy-levomilnacipran. Both oxidative metabolites undergo further conjugation with glucuronide to form conjugates. The desethylation is catalyzed primarily by CYP3A4 with minor contribution by CYP2C8, 2C19, 2D6, and 2J2.

Excretion

Levomilnacipran and its metabolites are eliminated primarily by renal excretion. Following oral administration of 14C-levomilnacipran solution, approximately 58% of the dose is excreted in urine as unchanged levomilnacipran. N-desethyl levomilnacipran is the major metabolite excreted in the urine and accounted for approximately 18% of the dose. Other identifiable metabolites excreted in the urine are levomilnacipran glucuronide (4%), desethyl levomilnacipran glucuronide (3%), p-hydroxy levomilnacipran glucuronide (1%), and p-hydroxy levomilnacipran (1%). The metabolites are inactive [see Dosage and Administration (2.3)].

Drug Interaction Studies

Clinical Studies

The drug interaction studies for levomilnacipran are summarized in Figure 1.

Figure 1. PK Interactions between Levomilnacipran (LVM) and Other Drugs

In vitro Studies

In vitro studies suggested that CYP2C8, CYP2C19, CYP2D6, and CYP2J2 had minimal contributions to metabolism of levomilnacipran. In addition, levomilnacipran is not a substrate of BCRP, OATP1B1, OATP1B3, OAT1, OAT3, or OCT2 and is a weak substrate of P-gp.

In vitro studies have shown that levomilnacipran is not an inhibitor of CYP1A2, CYP2A6, CYP2C8, CYP2C9, CYP2C19, CYP2D6, CYP2E1, P-gp, OATP1B1, OATP1B3, OAT1, OAT3, or OCT2.

Alcohol

An in vitro study indicated increases of levomilnacipran release from FETZIMA extended-release capsules (20, 40, 80, and 120 mg) at 2 hours by approximately 9.5%, 23%, and 56% in the presence of 5%, 20%, and 40% (v/v) alcohol, respectively. Effect of 40% alcohol resulted in nearly complete drug release in 4 hours. There is no in vivo study conducted for the effect of alcohol on drug exposure.

Specific Populations

The effect of intrinsic patient factors on the pharmacokinetics of levomilnacipran is presented in Figure 2.

Figure 2 Effect of Intrinsic Factors on Levomilnacipran PK

13 NONCLINICAL TOXICOLOGY

13.1 Carcinogenesis, Mutagenesis, Impairment of Fertility

Carcinogenesis

Levomilnacipran administered by oral gavage to rats for 2 years and Tg.rasH2 mice for 6 months did not increase the incidence of tumors in either study.

Rats received levomilnacipran at doses up to 90/70 mg/kg/day (the dose was lowered in males after 45 weeks of dosing). The 90 mg/kg/day dose is 7 times the maximum recommended human dose (MRHD) of 120 mg on a mg/m^2 basis.

Tg.rasH2 mice received levomilnacipran at doses up to 150 mg/kg/day.

Mutagenesis

Levomilnacipran was not mutagenic in the in vitro bacterial mutation assay (Ames test) and was not clastogenic in an in vivo micronucleus assay in rats. Additionally, levomilnacipran was not genotoxic in the in vitro mouse lymphoma (L5178Y TK+/-) cell forward mutation assay.

Impairment of Fertility

When levomilnacipran was administered orally to male and female rats before mating, through mating and up to Day 7 of gestation at doses up to 100 mg/kg/day, no effects were observed on fertility. This dose is 8 times the MRHD on a mg/m^2 basis.

14 CLINICAL STUDIES

14.1 Treatment of Major Depressive Disorder

The efficacy of FETZIMA for the treatment of major depressive disorder (MDD) was established in three 8-week randomized, double-blind, placebo-controlled studies (at doses 40-120 mg once daily) in adult (18 - 78 years of age) outpatients who met the Diagnostic and Statistical Manual of Mental Disorders (DSM-IV-TR) criteria for MDD. Two of the studies were fixed dose (Study 1 and Study 2) and one study was flexible dose (Study 3).

In Study 1, patients received 40 mg (n = 178), 80 mg (n = 179), or 120 mg (n = 180) of FETZIMA once daily, or placebo (n = 176). In Study 2, patients received either 40 mg (n = 188) or 80 mg (n = 188) of FETZIMA once daily, or placebo (n = 186). In the flexible-dose study (Study 3), patients received 40 to 120 mg (n = 217) of FETZIMA once daily, or placebo (n = 217) with 21%, 34%, and 44% of FETZIMA patients on 40 mg, 80 mg, and 120 mg, respectively at the end of their treatment.

In all three studies, FETZIMA demonstrated superiority over placebo in the improvement of depressive symptoms as measured by the Montgomery-Asberg Depression Rating Scale (MADRS) total score (see Table 6). FETZIMA also demonstrated superiority over placebo as measured by improvement in the Sheehan Disability Scale (SDS) functional impairment total score.

Table 6 Summary of Results for the Primary Efficacy Endpoint MADRS
Study Number | Treatment Group | Mean Baseline Score (SD) | LS Mean Change from Baseline (SE) | Placebo-subtracted Differencea (95% CI)
Study 1 (fixed dose) | FETZIMA (ER 40 mg/day)* | 36.0 (4.1) | -14.8 (1.0) | -3.2 (-5.9, -0.5)
 | FETZIMA (ER 80 mg/day)* | 36.1 (3.9) | -15.6 (1.0) | -4.0 (-6.7, -1.3)
 | FETZIMA (ER 120 mg/day)* | 36.0 (3.9) | -16.5 (1.0) | -4.9 (-7.6, -2.1)
 | Placebo | 35.6 (4.5) | -11.6 (1.0) | --
Study 2 (fixed-dose) | FETZIMA (ER 40 mg/day)* | 30.8 (3.4) | -14.6 (0.8) | -3.3 (-5.5, -1.1)
 | FETZIMA (ER 80 mg/day)* | 31.2 (3.5) | -14.4 (0.8) | -3.1 (-5.3, -1.0)
 | Placebo | 31.0 (3.8) | -11.3 (0.8) | --
Study 3 (flexible-dose) | FETZIMA (ER 40 - 120 mg/day)* | 35.0 (3.6) | -15.3 (0.8) | -3.1 (-5.3, -0.9)
 | Placebo | 35.2 (3.8) | -12.2 (0.8) | --
SD: standard deviation; SE: standard error; LS Mean: least-squares mean; CI: confidence interval unadjusted for multiplicity.
a Difference (drug minus placebo) in least-squares mean change from baseline to endpoint (Week 8).
* Doses statistically significantly superior to placebo.

Post-hoc analyses of the relationships between treatment outcome and age, gender, and race did not suggest any differential responsiveness on the basis of these patient characteristics.

In a maintenance study (Study 4; NCT02288325), adult patients meeting DSM-5 criteria for MDD received flexibly dosed FETZIMA (40 mg, 80 mg, or 120 mg) once daily for 8 weeks. Responders in the initial 8-week treatment period were eligible to enter a 12-week, open-label, fixed-dose stabilization phase. At the end of stabilization, approximately half of the subjects were receiving 120 mg once daily. Three hundred twenty-four (324) patients who met the response criteria (MADRS total score ≤12) after 20 weeks of open-label treatment were randomized to the double-blind treatment phase with FETZIMA or placebo for 26 weeks. The primary efficacy endpoint was the time from randomization to first relapse during the double-blind phase. Relapse of depressive episode was defined as a MADRS total score ≥ 18 at two consecutive visits or insufficient therapeutic response as judged by the investigator. Patients on FETZIMA experienced a statistically significantly longer time to relapse than patients on placebo (Figure 3).

Figure 3. Kaplan-Meier Estimated Proportion of Patients with Relapse for Adults with MDD (Study 4)

16 HOW SUPPLIED/STORAGE AND HANDLING

FETZIMA extended-release capsules are supplied in the following configurations:

Capsule Strength | Capsule Color/Shape | Capsule Markings | Package Configuration | NDC Code
20 mg | yellow cap white body | black "FL" on cap black "20" on body | Bottle / 30 count | 0456-2220-30
 |  |  | Hospital Unit Dose (Blister) / 10 x 10 | 0456-2220-63
40 mg | yellow cap yellow body | black "FL" on cap black "40" on body | Bottle / 30 count | 0456-2240-30
 |  |  | Bottle / 90 count | 0456-2240-90
 |  |  | Hospital Unit Dose (Blister) / 10 x 10 | 0456-2240-63
80 mg | pink cap white body | black "FL" on cap black "80" on body | Bottle / 30 count | 0456-2280-30
 |  |  | Bottle / 90 count | 0456-2280-90
 |  |  | Hospital Unit Dose (Blister) /10 x 10 | 0456-2280-63
120 mg | pink cap pink body | black "FL" on cap black "120" on body | Bottle / 30 count | 0456-2212-30
 |  |  | Bottle / 90 count | 0456-2212-90
 |  |  | Hospital Unit Dose (Blister) / 10 x 10 | 0456-2212-63

FETZIMA Titration Pack is supplied in the following configuration:

Capsule Strength | Capsule Color/Shape | Capsule Markings | Package Configuration | NDC Code
20 mg | yellow cap white body | black "FL" on cap black "20" on body | Titration Pack (Blister) containing two 20 mg capsules and twenty-six 40 mg capsules | 0456-2202-28
40 mg | yellow cap yellow body | black "FL" on cap black "40" on body

Storage and Handling

All package configurations: Store at 25°C (77°F); excursions permitted between 15°C and 30°C (59°F and 86°F) [See USP Controlled Room Temperature].

17 PATIENT COUNSELING INFORMATION

Advise the patient to read the FDA-approved patient labeling (Medication Guide).

Suicide Thoughts and Behaviors

Advise patients and caregivers to look for the emergence of suicidal thoughts and behaviors, especially early during treatment and when the dose is adjusted up or down, and instruct them to report such symptoms to the healthcare provider [see Boxed Warning and Warnings and Precautions (5.1)].

Dosing and Administration

Advise patients that FETZIMA should be swallowed whole and should not be chewed, crushed, or opened.

Advise patients that FETZIMA can be taken with or without food.

Instruct patients if they miss a dose, to take the missed dose as soon as they remember. If it is almost time for the next dose, instruct them to skip the missed dose and take their next dose at the regular time. Advise them not to take two doses of FETZIMA at the same time.

Concomitant Medication

Instruct patients not to take FETZIMA with an MAOI or within 14 days of stopping an MAOI and to allow 7 days after stopping FETZIMA before starting an MAOI [see Contraindications (4)]. Advise patients to inform their physician if they are taking, or plan to take, any prescription or over-the-counter drugs, since there is a potential for drug-drug interactions [see Drug Interactions (7.1)].

Allergic Reactions

Advise patients to notify their healthcare provider if they develop an allergic reaction such as rash, hives, swelling, or difficulty breathing [see Contraindications (4)].

Serotonin Syndrome

Caution patients about the risk of serotonin syndrome, particularly with the concomitant use of FETZIMA with other serotonergic agents (including triptans, tricyclic antidepressants, opioids, lithium, amphetamines, tryptophan, buspirone, and St. John’s Wort supplements) [see Warnings and Precautions (5.2) and Drug Interactions (7.1)]. Instruct patients to contact their health care provider or report to the emergency room if they experience signs or symptoms of serotonin syndrome.

Elevated Blood Pressure and Heart Rate

Advise patients that they should have regular monitoring of blood pressure and heart rate when taking FETZIMA [see Warnings and Precautions (5.3, 5.4)].

Increased Risk of Bleeding

Caution patients about the concomitant use of FETZIMA and NSAIDs, aspirin, warfarin, or other drugs that affect coagulation because combined use has been associated with an increased risk of bleeding. Advise patients to inform their healthcare provider if they are taking or planning to take any prescription or over-the-counter medications that increase the risk of bleeding [see Warnings and Precautions (5.5)].

Angle Closure Glaucoma

Patients should be advised that taking FETZIMA can cause mild pupillary dilation, which in susceptible individuals, can lead to an episode of angle closure glaucoma [see Warnings and Precautions (5.6)].

Urinary Hesitation or Retention

Caution patients about the risk of urinary hesitation and retention while taking FETZIMA, particularly in patients prone to obstructive urinary disorders. Instruct patients to consult with their healthcare provider if they develop any problems with urine flow [see Warnings and Precautions (5.7)].

Activation of Mania/Hypomania

Advise patients and their caregivers to look for signs of activation of mania/hypomania [see Warnings and Precautions (5.8)].

Seizures

Caution patients about using FETZIMA if they have a history of a seizure disorder [see Warnings and Precautions (5.9)].

Discontinuation Syndrome

Advise patients not to abruptly stop taking FETZIMA without first talking with their healthcare provider. Patients should be aware that discontinuation effects may occur when suddenly stopping FETZIMA and they should monitor for discontinuation symptoms [see Warnings and Precautions (5.10)].

Hyponatremia

Advise patients that hyponatremia has been reported as a result of treatment with FETZIMA. Advise patients of the signs and symptoms of hyponatremia [see Warnings and Precautions (5.11)].

Sexual Dysfunction

Advise patients that use of FETZIMA may cause symptoms of sexual dysfunction in both male and female patients. Inform patients that they should discuss any changes in sexual function and potential management strategies with their healthcare provider [see Warnings and Precautions (5.12)].

Alcohol

Advise patients to avoid consumption of alcohol while taking FETZIMA [see Drug Interactions (7.1), Clinical Pharmacology (12.3)].

Pregnancy

- Advise pregnant females to notify their healthcare provider if they become pregnant or intend to become pregnant during treatment with FETZIMA.
- Advise patients that FETZIMA may increase the risk of neonatal complications requiring prolonged hospitalization, respiratory support, tube feeding.
- Advise patient that there is a pregnancy exposure registry that monitors pregnancy outcomes in women exposed to FETZIMA during pregnancy [see Use in Specific Populations (8.1)]

Lactation

Advise breastfeeding patients using FETZIMA to monitor infants for sedation, agitation, irritability, poor feeding, and poor weight gain and to seek medical care if they notice these signs [see Use in Specific Populations (8.2)].

Interference with Cognitive and Motor Performance

Caution patients about operating hazardous machinery, including automobiles, until they are reasonably certain that FETZIMA therapy does not adversely affect their ability to engage in such activities.

Distributed by:

AbbVie, Inc.
1 N Waukegan Rd.
North Chicago, IL 60064

©2024 AbbVie. All rights reserved.
FETZIMA and its design are trademarks of Pierre Fabre Medicament.
Licensed from Pierre Fabre Medicament.

20085454

MEDICATION GUIDE
FETZIMA® (fet-ZEE-muh)
(levomilnacipran)
extended-release capsules, for oral use

What is the most important information I should know about FETZIMA?
FETZIMA may cause serious side effects, including:

- Increased risk of suicidal thoughts and actions. FETZIMA and other antidepressant medicines may increase suicidal thoughts and actions in some people 24 years and younger, especially within the first few months of treatment or when the dose is changed. FETZIMA is not for use in children.
  - Depression or other mental illnesses are the most important causes of suicidal thoughts or actions.

How can I watch for and try to prevent suicidal thoughts and actions?

- Pay close attention to any changes, especially sudden changes in mood, behavior, thoughts, or feelings, or if you develop suicidal thoughts or actions. This is very important when an antidepressant medicine is started or when the dose is changed.
- Call your healthcare provider right away to report new or sudden changes in mood, behavior, thoughts, or feelings or if you develop suicidal thoughts or actions.
- Keep all follow-up visits with your healthcare provider as scheduled. Call your healthcare provider between visits as needed, especially if you have concerns about symptoms.

Call your healthcare provider or get emergency medical help right away if you or your family member have any of the following symptoms, especially if they are new, worse, or worry you:

● attempts to commit suicide

● acting on dangerous impulses

● acting aggressive, being angry or violent

● thoughts about suicide or dying

● new or worse depression

● new or worsening anxiety

● panic attacks

● feeling very agitated or restless

● new or worse irritability

● trouble sleeping

● an extreme increase in activity or talking (mania)

● other unusual changes in behavior or mood

What is FETZIMA?
FETZIMA is a prescription medicine used to treat a certain type of depression called Major Depressive Disorder (MDD) in adults.
It is not known if FETZIMA is safe and effective for use in children.
It is not known if FETZIMA is safe and effective for the management of fibromyalgia. FETZIMA is not for use for the management of fibromyalgia.

Do not take FETZIMA if you:

- are allergic to levomilnacipran, milnacipran HCl, or any of the ingredients in FETZIMA. See the end of this Medication Guide for a complete list of ingredients in FETZIMA.
- are taking or have taken within the last 14 days, a medicine called a monoamine oxidase inhibitor (MAOI), including the antibiotic linezolid or intravenous methylene blue.

Ask your healthcare provider or pharmacist if you are not sure if you take an MAOI, including the antibiotic linezolid or intravenous methylene blue.
Do not start taking an MAOI for at least 7 days after you stop treatment with FETZIMA.

Before taking FETZIMA, tell your healthcare provider about all your medical conditions, including if you:

- have or have a family history of suicide, depression, bipolar disorder, mania, or hypomania
- have high blood pressure
- have or had heart problems, including fast heartbeat, or stroke
- have or had bleeding problems
- have glaucoma (high pressure in the eye)
- have or had problems urinating (hesitation) or emptying your bladder (retention)
- have or had seizures (convulsions)
- have low sodium levels in your blood
- have or had kidney problems
- drink alcohol
- are pregnant or plan to become pregnant. FETZIMA may harm your unborn baby. Taking FETZIMA during your third trimester of pregnancy may cause you to have an increased risk of bleeding after your delivery and may also cause your baby to be at increased risk for withdrawal symptoms, or breathing, temperature control, feeding or other problems at birth. Talk to your healthcare provider about the risks to you and your baby if you take FETZIMA during pregnancy.
  - Tell your healthcare provider right away if you become pregnant or think you may be pregnant during treatment with FETZIMA.
  - There is a pregnancy registry for women who are exposed to FETZIMA during pregnancy. The purpose of the registry is to collect information about the health of women exposed to FETZIMA and their baby. If you become pregnant during treatment with FETZIMA, talk to your healthcare provider about registering with the National Pregnancy Registry for Antidepressants at 1-844-405-6185 or visit online at https://womensmentalhealth.org/research/pregnancyregistry/antidepressants.
- are breastfeeding or plan to breastfeed. It is not known if FETZIMA passes into your breast milk. Talk to your healthcare provider about the best way to feed your baby during treatment with FETZIMA.
  - If you breastfeed during treatment with FETZIMA, call your healthcare provider if your baby develops sleepiness or fussiness, or is not feeding or gaining weight well.

Tell your healthcare provider about all the medicines you take, including prescription and over-the-counter medicines, vitamins, and herbal supplements.
FETZIMA and other medicines may affect each other causing possible serious side effects.
FETZIMA may affect the way other medicines work and other medicines may affect the way FETZIMA works.
Especially tell your healthcare provider if you take:

- MAOIs
- medicines used to treat migraine headache known as triptans
- tricyclic antidepressants
- lithium
- tramadol, fentanyl, meperidine, methadone, or other opioids
- tryptophan
- buspirone
- amphetamines
- St. John’s Wort
- medicines that can affect blood clotting such as aspirin, nonsteroidal anti-inflammatory drugs (NSAIDs) and warfarin
- diuretics
- medicines used to treat mood, anxiety, psychotic or thought disorders, including selective serotonin reuptake inhibitors (SSRIs) and serotonin norepinephrine reuptake inhibitors (SNRIs)

Ask your healthcare provider if you are not sure if you are taking any of these medicines. Your healthcare provider can tell you if it is safe to take FETZIMA with your other medicines.
Do not start or stop any other medicines during treatment with FETZIMA without talking to your healthcare provider first. Stopping FETZIMA suddenly may cause you to have serious side effects. See, “What are the possible side effects of FETZIMA?”
Know the medicines you take. Keep a list of them to show your healthcare provider and pharmacist when you get a new medicine.

How should I take FETZIMA?

- Take FETZIMA exactly as your healthcare provider tells you to take it. Do not change your dose or stop taking FETZIMA without first talking to your healthcare provider.
- Your healthcare provider may need to change the dose of FETZIMA until it is the right dose for you.
- Take FETZIMA 1 time each day at about the same time each day.
- Take FETZIMA with or without food.
- Swallow FETZIMA capsules whole. Do not open, chew, or crush the FETZIMA capsule.
- If you miss a dose of FETZIMA, take the missed dose as soon as you remember. If it is almost time for the next dose, skip the missed dose and take your next dose at the regular time. Do not take 2 doses of FETZIMA at the same time.
- If you take too much FETZIMA, call your healthcare provider or poison control center at 1-800-222-1222, or go to the nearest hospital emergency room right away.

What should I avoid while taking FETZIMA?

- Do not drive, operate heavy machinery, or do other dangerous activities until you know how FETZIMA affects you. FETZIMA can cause sleepiness or may affect your ability to make decisions, think clearly, or react quickly.
- Avoid drinking alcohol during treatment with FETZIMA.

What are the possible side effects of FETZIMA?
FETZIMA may cause serious side effects, including:

- See “What is the most important information I should know about FETZIMA?”
- Serotonin syndrome. A potentially life-threatening problem called serotonin syndrome can happen when FETZIMA is taken with certain other medicines. See “Do not take FETZIMA if you.” Call your healthcare provider or go to the nearest hospital emergency room right away if you have any of the following signs and symptoms of serotonin syndrome:

○ agitation

○ seeing or hearing things that are not real (hallucinations)

○ confusion

○ coma

○ fast heartbeat

○ blood pressure changes

○ dizziness

○ sweating

○ flushing

○ high body temperature (hyperthermia)

○ tremors, stiff muscles, or muscle twitching

○ loss of coordination

○ seizures

○ nausea, vomiting, diarrhea

- High blood pressure (hypertension). Your healthcare provider should check your blood pressure before you start and during treatment with FETZIMA. If you have high blood pressure, it should be controlled before you start treatment with FETZIMA.
- Increased heart rate. Your healthcare provider should check your heart rate before you start and during treatment with FETZIMA. If you have heart problems or problems with an abnormal heartbeat, your problems should be treated before you start treatment with FETZIMA.
- Increased risk of bleeding. Taking FETZIMA with aspirin, non-steroidal anti-inflammatory drugs (NSAIDs), warfarin or blood thinners may add to this risk. Tell your healthcare provider right away about any unusual bleeding or bruising.
- Eye problems (angle-closure glaucoma). FETZIMA may cause a type of eye problem called angle-closure glaucoma in people with certain eye problems. You may want to undergo an eye examination to see if you are at risk and receive preventative treatment if you are. Call your healthcare provider if you have changes in your vision, eye pain, or swelling or redness in or around the eye.
- Problems with urination. FETZIMA may cause you to have problems with urination including decreased urine flow and being unable to pass any urine. Tell your healthcare provider if you develop any problems with urine flow during treatment with FETZIMA.
- Manic episodes. Manic episodes may happen in people with bipolar disorder who take FETZIMA. Symptoms may include:

○ greatly increased energy

○ severe trouble sleeping

○ racing thoughts

○ reckless behavior

○ unusually grand ideas

○ excessive happiness or irritability

○ talking more or faster than usual

- Seizures (convulsions).
- Discontinuation syndrome. Suddenly stopping FETZIMA may cause you to have serious side effects. Your healthcare provider may want to decrease your dose slowly. Symptoms may include:

○ changes in your mood

○ headache

○ irritability and agitation

○ tiredness

○ dizziness

○ problems sleeping

○ electric shock sensation (paresthesia)

○ hypomania

○ anxiety

○ ringing in your ears (tinnitus)

○ confusion

○ seizures

- Low sodium levels in your blood (hyponatremia). Low sodium levels in your blood that may be serious and may cause death can happen during treatment with FETZIMA. Elderly people and people who take certain medicines may be at greater risk for this. Signs and symptoms may include:

○ headache

○ difficulty concentrating

○ memory changes

○ confusion

○ weakness and unsteadiness on your feet which can lead to falls

In more severe or more sudden cases, signs and symptoms include:

○ hallucinations (seeing or hearing things that are not real)

○ fainting

○ seizures

○ coma

○ stopping breathing (respiratory arrest)

- Sexual problems (dysfunction). Taking FETZIMA may cause sexual problems.

Symptoms in males may include:

○ delayed ejaculation or inability to have an ejaculation
○ decreased sex drive

○ problems getting or keeping an erection

Symptoms in females may include:

○ decreased sex drive

○ delayed orgasm or inability to have an orgasm

Talk to your healthcare provider if you develop any changes in your sexual function or if you have any questions or concerns about sexual problems during treatment with FETZIMA. There may be treatments your healthcare provider can suggest.

The most common side effects of FETZIMA, include:

● nausea

● problems getting or keeping an erection

● constipation

● delayed ejaculation or inability to have an ejaculation

● sweating

● vomiting

● increased heart rate

● fast or irregular heartbeat (palpitations)

These are not all the possible side effects of FETZIMA.
Call your doctor for medical advice about side effects. You may report side effects to FDA at 1-800-FDA-1088.

How should I store FETZIMA?

- Store FETZIMA at room temperature between 68°F to 77°F (20°C to 25°C).
- Keep FETZIMA and all medicines out of the reach of children.

General information about the safe and effective use of FETZIMA
Medicines are sometimes prescribed for purposes other than those listed in a Medication Guide. Do not use FETZIMA for a condition for which it was not prescribed. Do not give FETZIMA to other people, even if they have the same symptoms that you have. It may harm them. You can ask your pharmacist or healthcare provider for information about FETZIMA that is written for healthcare professionals.

What are the ingredients in FETZIMA?
Active ingredient: levomilnacipran hydrochloride
Inactive ingredients: ethylcellulose, hypromellose, povidone, sugar spheres, talc, titanium dioxide, triethyl citrate, black iron oxide, red iron oxide (80 mg and 120 mg capsules only) shellac glaze, yellow iron oxide (20 mg and 40 mg capsules only)
Distributed by:
AbbVie, Inc.
1 N Waukegan Rd.
North Chicago, IL 60064
©2023 AbbVie. All rights reserved.
For more information, go to www.FETZIMA.com or call 1-800-678-1605.

This Medication Guide has been approved by the U.S. Food and Drug Administration. Revised: 8/2023

20085454

PRINCIPAL DISPLAY PANEL

Rx only NDC 0456-2220-30
Fetzima®
levomilnacipran
extended-release capsules
20 mg per capsule
Dispense the accompanying
Medication Guide to each patient.
30 capsules

PRINCIPAL DISPLAY PANEL

Rx only NDC 0456-2240-30
Fetzima®
levomilnacipran
extended-release capsules
40 mg per capsule

Dispense the accompanying
Medication Guide to each patient.
30 capsules

PRINCIPAL DISPLAY PANEL

Rx only NDC 0456-2280-30
Fetzima®
levomilnacipran
extended-release capsules
80 mg per capsule
Dispense the accompanying
Medication Guide to each patient.
30 capsules

PRINCIPAL DISPLAY PANEL

Rx only NDC 0456-2212-30
Fetzima®
levomilnacipran
extended-release capsules
120 mg per capsule

Dispense the accompanying
Medication Guide to each patient.
30 capsules

PRINCIPAL DISPLAY PANEL

Rx Only NDC 0456-2202-28
Fetzima®
levomilnacipran
extended-release capsules
Titration Pack
Two 20 mg Capsules

Take one 20 mg capsule once daily

On Day 1 and Day 2.
Twenty-six 40 mg capsules

Take one 40 mg capsule once daily

On Day 3 through Day 28.

Patients: Lift up flap to find Instructions for sliding out the tray.

Dispense the accompanying Medication Guide to each patient.

PRINCIPAL DISPLAY PANEL

Rx Only NDC 0456-2200-07
Professional Sample-Not for Sale

Fetzima®
levomilnacipran
extended-release capsules
Two 20 mg Capsules

Take one 20 mg capsule once daily

On Day 1 and Day 2.
Five 40 mg capsules

Take one 40 mg capsule once daily

On Day 3 through Day 7.

Dispense the accompanying Medication Guide to each patient.